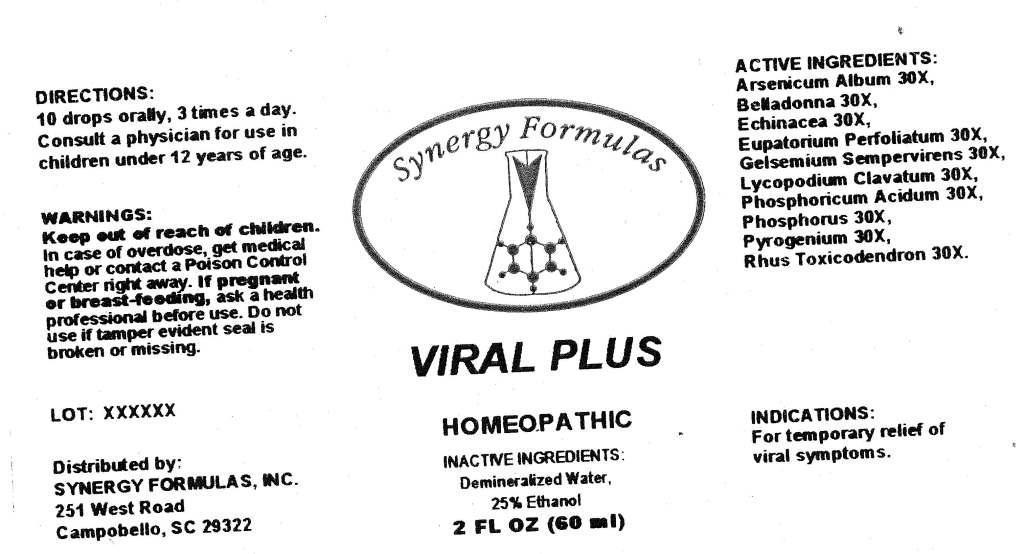 DRUG LABEL: Viral Plus
NDC: 43772-0008 | Form: LIQUID
Manufacturer: Synergy Formulas, Inc.
Category: homeopathic | Type: HUMAN OTC DRUG LABEL
Date: 20130402

ACTIVE INGREDIENTS: ARSENIC TRIOXIDE 30 [hp_X]/1 mL; ATROPA BELLADONNA WHOLE 30 [hp_X]/1 mL; ECHINACEA, UNSPECIFIED 30 [hp_X]/1 mL; EUPATORIUM PERFOLIATUM FLOWERING TOP 30 [hp_X]/1 mL; GELSEMIUM SEMPERVIRENS ROOT 30 [hp_X]/1 mL; LYCOPODIUM CLAVATUM SPORE 30 [hp_X]/1 mL; PHOSPHORIC ACID 30 [hp_X]/1 mL; PHOSPHORUS 30 [hp_X]/1 mL; RANCID BEEF 30 [hp_X]/1 mL; TOXICODENDRON PUBESCENS LEAF 30 [hp_X]/1 mL
INACTIVE INGREDIENTS: WATER; ALCOHOL

Drug Facts

ACTIVE INGREDIENTS

Arsenicum Album 30X, Belladonna 30X, Echinacea 30X, Eupatorium Perfoliatum 30X, Gelsemium Sempervirens 30X, Lycopodium Clavatum 30X, Phosphoricum Acidum 30X, Phosphorus 30X, Pyrogenium 30X, Rhus Toicodendron 30X

INDICATIONS

For temporary relief of viral symptoms.

WARNINGS

Keep out of reach of children. In case of overdose, get medical help or contact a Poison Control Center right away. If pregnant or breast-feeding, ask a health professional before use. Do not use if tamper evident seal is broken or missing.

DIRECTIONS

10 drops orally, 3 times a day. Consult a physician for use in children under 12 years of age.

INACTIVE INGREDIENTS

Demineralized Water, 25% Ethanol

KEEP OUT OF REACH OF CHILDREN

In case of overdose, get medical help or contact a Poison Control Center right away.

INDICATIONS AND USAGE

For temporary relief of viral symptoms.

QUESTIONS

Distributed by:

SYNERGY FORMULAS, INC.

251 West Road

Campobello, SC 29322

PACKAGE LABEL

Synergy Formulas

VIRAL PLUS

HOMEOPATHIC

2 FL OZ (60 ml)